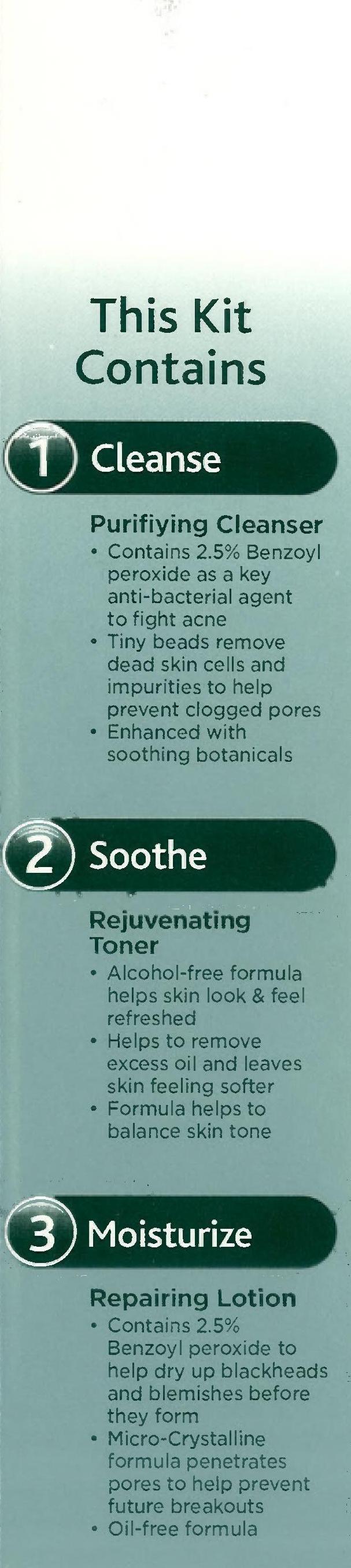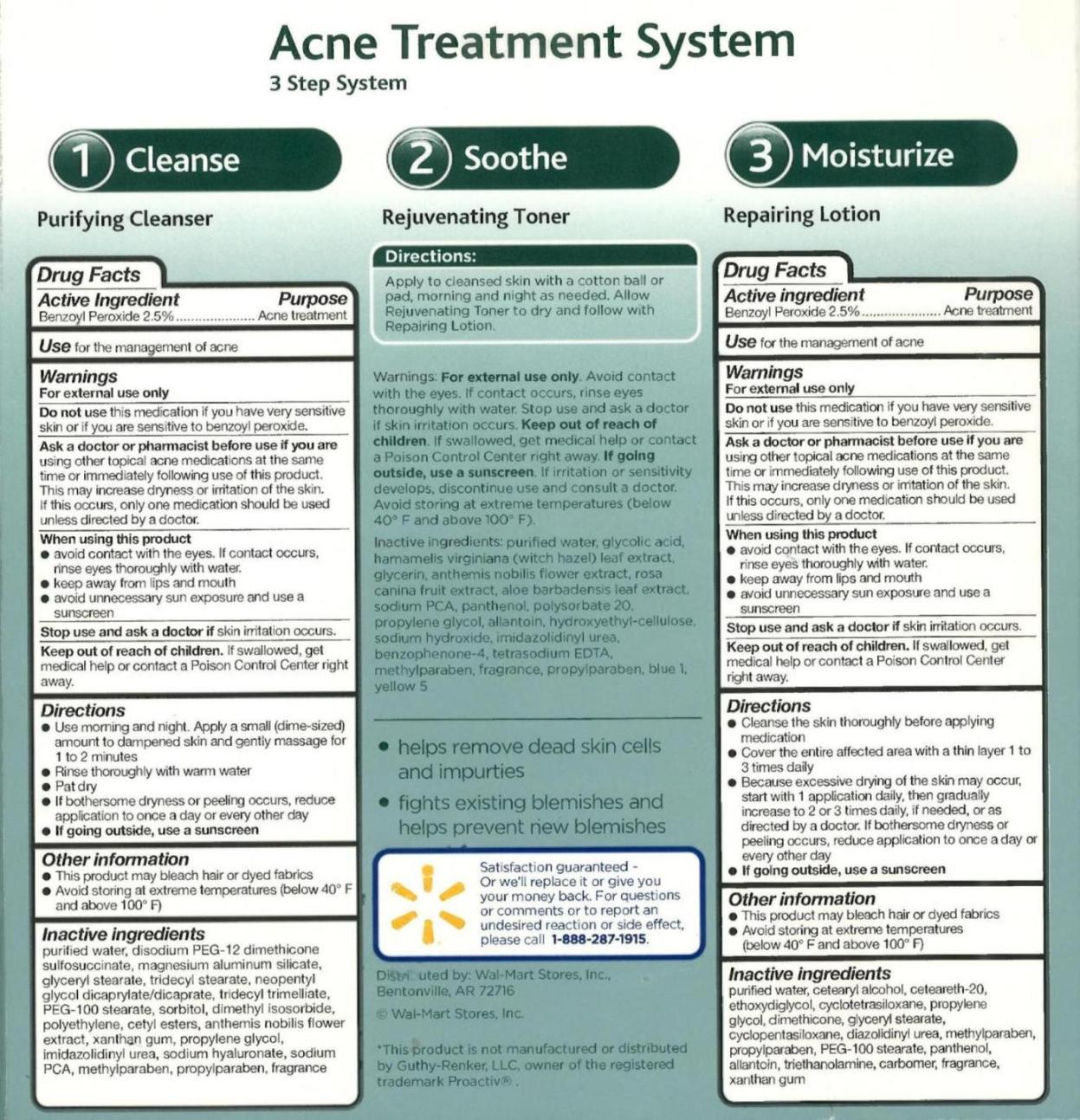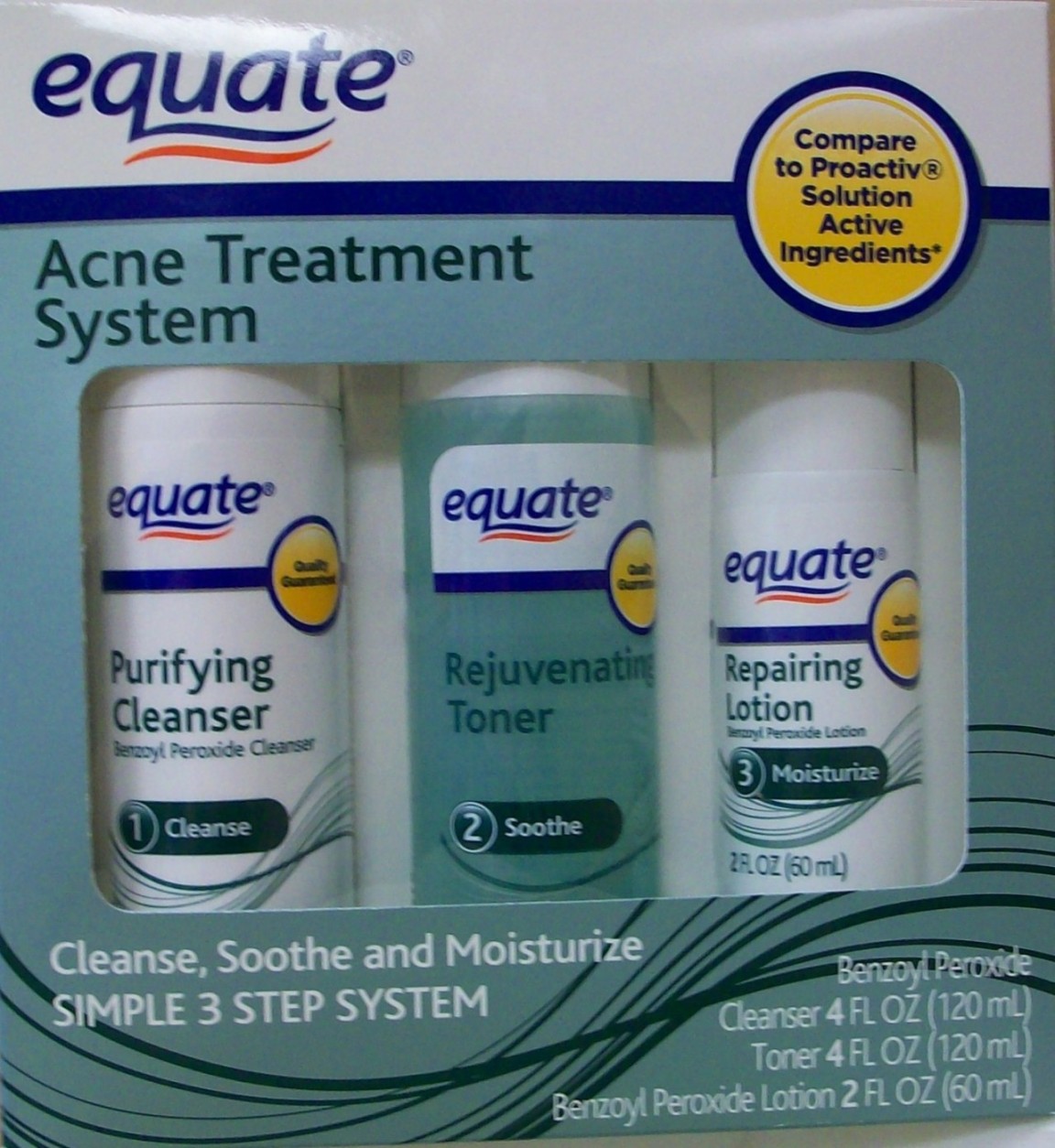 DRUG LABEL: BENZOYL PEROXIDE
NDC: 49035-021 | Form: KIT | Route: TOPICAL
Manufacturer: Wal-Mart Stores Inc
Category: otc | Type: HUMAN OTC DRUG LABEL
Date: 20110204

ACTIVE INGREDIENTS: BENZOYL PEROXIDE 36.9 mg/1 mL; BENZOYL PEROXIDE 36.9 mg/1 mL
INACTIVE INGREDIENTS: WATER; MAGNESIUM ALUMINUM SILICATE; GLYCERYL MONOSTEARATE; POLYOXYL 100 STEARATE; PEG-12 STEARATE; SORBITOL; DIMETHYL ISOSORBIDE; TRIDECYL STEARATE; NEOPENTYL GLYCOL; HIGH DENSITY POLYETHYLENE; CETYL ESTERS WAX; CHAMAEMELUM NOBILE FLOWER; HYALURONATE SODIUM; SODIUM PYRROLIDONE CARBOXYLATE; XANTHAN GUM; IMIDUREA; METHYLPARABEN; PROPYLPARABEN; Water; DIETHYLENE GLYCOL MONOETHYL ETHER; POLYOXYL 20 CETOSTEARYL ETHER; CETOSTEARYL ALCOHOL; PROPYLENE GLYCOL; DIMETHICONE; GLYCERYL MONOSTEARATE; METHYLPARABEN; DIAZOLIDINYL UREA; PROPYLPARABEN; PANTHENOL; ALLANTOIN; XANTHAN GUM; CARBOMER HOMOPOLYMER TYPE C; POLYOXYL 100 STEARATE; TROLAMINE

drug facts

ACTIVE INGREDIENT

Purifying Cleanser
Active ingredient Purpose
Benzoyl Peroxide 2.5%..............Acne Treatment

PURPOSE

Purifying Cleanser
Active ingredient Purpose
Benzoyl Peroxide 2.5%..............Acne Treatment
Use for the management of acne

KEEP OUT OF REACH OF CHILDREN

Purifying Cleanser Warning Section
Warnings
For external use only
Do not use this medication if you have very sensitive
skin or if you are very sensitive to benzoyl peroxide.
Ask a doctor or pharmacist before use if you are
using other topical acne medications at the same
time or immediately following use of this product.
This may increase dryness or irritation of the skin.
If this occurs, only one medication should be used
unless directed by a doctor.
When using this product
- avoid contact with the eyes. If contact occurs,
rinse eyes thoroughly with water.
- keep away from lips and mouth
- aviod unnecessary sun exposure and use a
sunscreen
Stop use and ask a doctor if skin irritation occurs.
Keep out of the reach of children. If swallowed, get
medical help or contact a Poison Control Center right
away.

INDICATIONS AND USAGE

Purifying Cleanser Directions Section

Directions

- Use morning and night. Apply a small (dime sized)
amount to dampened skin and gently massage for
1 to 2 minutes.
- Rinse thoroughly with warm water
- Pat dry
- If bothersome dryness or peeling occurs, reduce
application to once a day or every other day

- If going outside, use a sunscreen

Other information

- This product may bleach hair or dyed fabrics
- Avoid storing at extreme temperatures (below 40
degrees F and above 100 degrees F)

WARNINGS

Purifying Cleanser Warning Section
Warnings
For external use only
Do not use this medication if you have very sensitive
skin or if you are very sensitive to benzoyl peroxide.
Ask a doctor or pharmacist before use if you are
using other topical acne medications at the same
time or immediately following use of this product.
This may increase dryness or irritation of the skin.
If this occurs, only one medication should be used
unless directed by a doctor.
When using this product
- avoid contact with the eyes. If contact occurs,
rinse eyes thoroughly with water.
- keep away from lips and mouth
- aviod unnecessary sun exposure and use a
sunscreen
Stop use and ask a doctor if skin irritation occurs.
Keep out of the reach of children. If swallowed, get
medical help or contact a Poison Control Center right
away.

DOSAGE AND ADMINISTRATION

Purifying Cleanser Directions Section

Directions

- Use morning and night. Apply a small (dime sized)
amount to dampened skin and gently massage for
1 to 2 minutes.
- Rinse thoroughly with warm water
- Pat dry
- If bothersome dryness or peeling occurs, reduce
application to once a day or every other day

- If going outside, use a sunscreen

Other information

- This product may bleach hair or dyed fabrics
- Avoid storing at extreme temperatures (below 40
degrees F and above 100 degrees F)

Purifying Cleanser inactive ingredients section
Inactive Ingredients
purified water, disodium PEG-12 dimethicone
sulfosuccinate, magnesium aluminum silicate,
gyyceryl stearate, tridecyl stearate, neopentyl
glycol dicaprylate/dicaprate, tridecyl trimelliate,
PEG-100 Stearate, sorbitol, dimethyl isosorbide,
polyethylene, cetyl esters, anthemis nobilis flower
extract, xanthan gum, propylene glycol,
imidazolidinyl urea, sodium hyaluronate, sodium
PCA, methylparaben, propylparaben, fragrance

ACTIVE INGREDIENT

Repairing Lotion
Active ingredient Purpose
Benzoyl Peroxide 2.5%..............Acne Treatment

PURPOSE

Repairing Lotion
Active ingredient Purpose
Benzoyl Peroxide 2.5%..............Acne Treatment
Use for the management of acne

KEEP OUT OF REACH OF CHILDREN

Repairing Lotion Warning Section
Warnings
For external use only
Do not use this medication if you have very sensitive
skin or if you are very sensitive to benzoyl peroxide.
Ask a doctor or pharmacist before use if you are
using other topical acne medications at the same
time or immediately following use of this product.
This may increase dryness or irritation of the skin.
If this occurs, only one medication should be used
unless directed by a doctor.
When using this product
- avoid contact with the eyes. If contact occurs,
rinse eyes thoroughly with water.
- keep away from lips and mouth
- aviod unnecessary sun exposure and use a
sunscreen
Stop use and ask a doctor if skin irritation occurs.
Keep out of the reach of children. If swallowed, get
medical help or contact a Poison Control Center right
away.

INDICATIONS AND USAGE

Repairing Lotion Directions Section

Directions

- Cleanse the skin thoroughly before applying
medication
- Cover the entire affected area with a thin layer 1 to
3 times daily
- Because excessive drying of the skin may occur,
start with 1 application daily, then gradually
increase to 2 or 3 times daily, if needed or as
directed by a doctor. If bothersome dryness or
peeling occurs, reduce application to once a day or
every other day
- If going outside, use a sunscreen
Other information
- This product may bleach hair or dyed fabrics
- Avoid storing at extreme temperatures
(below 40 degrees F and above 100 degrees F)

WARNINGS

Repairing Lotion Warning Section
Warnings
For external use only
Do not use this medication if you have very sensitive
skin or if you are very sensitive to benzoyl peroxide.
Ask a doctor or pharmacist before use if you are
using other topical acne medications at the same
time or immediately following use of this product.
This may increase dryness or irritation of the skin.
If this occurs, only one medication should be used
unless directed by a doctor.
When using this product
- avoid contact with the eyes. If contact occurs,
rinse eyes thoroughly with water.
- keep away from lips and mouth
- aviod unnecessary sun exposure and use a
sunscreen
Stop use and ask a doctor if skin irritation occurs.
Keep out of the reach of children. If swallowed, get
medical help or contact a Poison Control Center right
away.

DOSAGE AND ADMINISTRATION

Repairing Lotion Directions Section

Directions

- Cleanse the skin thoroughly before applying
medication
- Cover the entire affected area with a thin layer 1 to
3 times daily
- Because excessive drying of the skin may occur,
start with 1 application daily, then gradually
increase to 2 or 3 times daily, if needed or as
directed by a doctor. If bothersome dryness or
peeling occurs, reduce application to once a day or
every other day
- If going outside, use a sunscreen
Other information
- This product may bleach hair or dyed fabrics
- Avoid storing at extreme temperatures
(below 40 degrees F and above 100 degrees F)

Repairing Lotion inactive ingredients section
Inactive ingredients
purified water, cetearyl alcohol, ceteareth-20,
ethoxydiglycol, cyclotetrasiloxane, propylene
glycol, dimethicone, glyceryl stearate,
cyclopentasiloxane diazolidinyl urea, methylparaben,
propylparaben, PEG-100 stearate, panthenol,
allantoin, triethanolamine, carbomer, fragrance,
xanthan gum